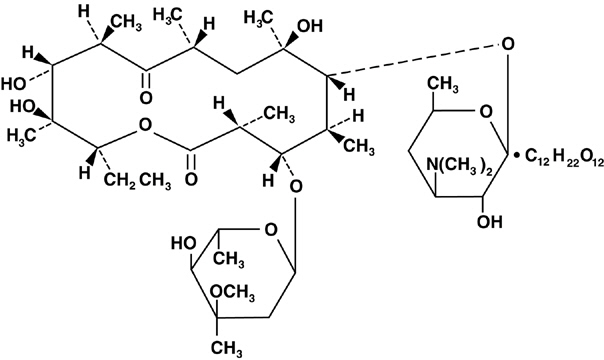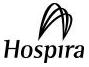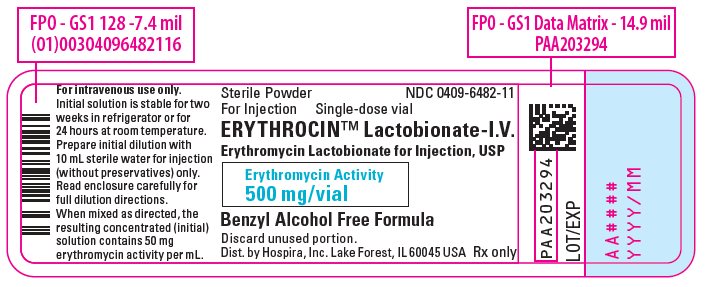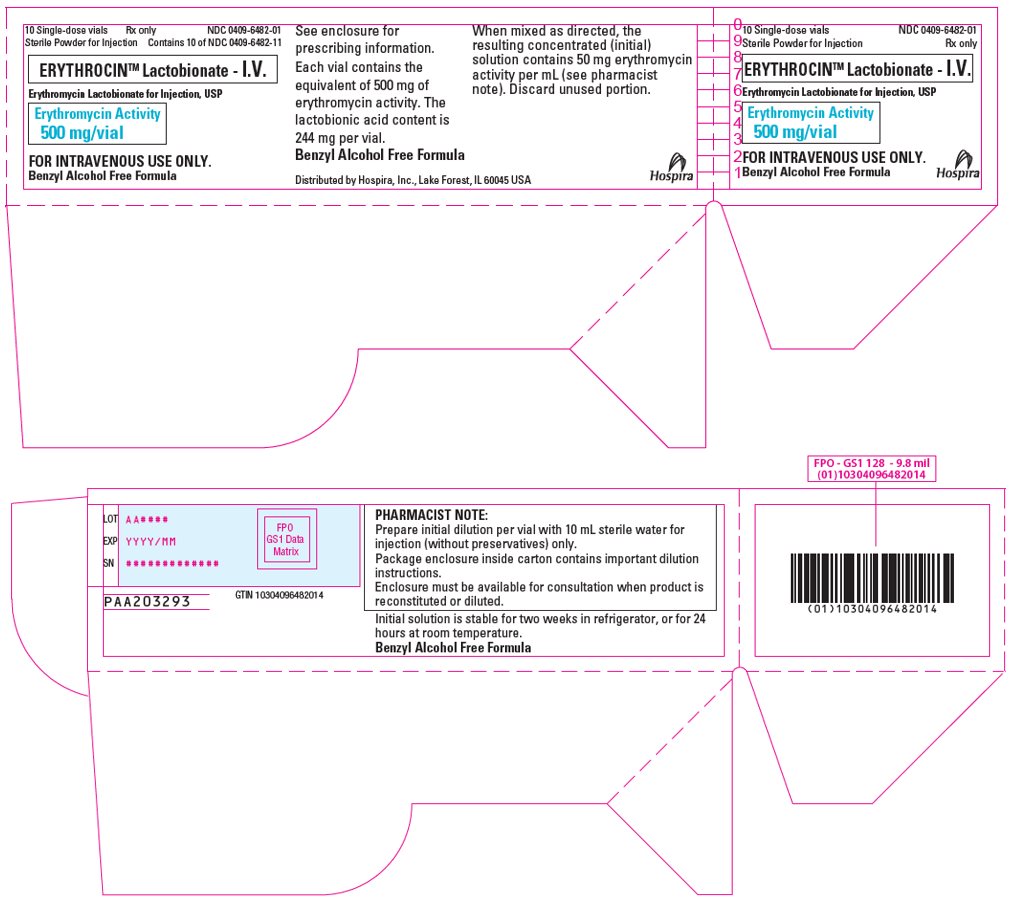 DRUG LABEL: Erythrocin Lactobionate
NDC: 0409-6482 | Form: INJECTION, POWDER, LYOPHILIZED, FOR SOLUTION
Manufacturer: Hospira, Inc.
Category: prescription | Type: HUMAN PRESCRIPTION DRUG LABEL
Date: 20251030

ACTIVE INGREDIENTS: ERYTHROMYCIN LACTOBIONATE 500 mg/10 mL
INACTIVE INGREDIENTS: WATER

Erythrocin™ Lactobionate - IV

Erythromycin Lactobionate for Injection, USP

INTRAVENOUS USE ONLY

Single-Dose Vials

Rx only

To reduce the development of drug-resistant bacteria and maintain the effectiveness of erythromycin and other antibacterial drugs, erythromycin should be used only to treat or prevent infections that are proven or strongly suspected to be caused by bacteria.

DESCRIPTION

Erythromycin is produced by a strain of Streptomyces erythraeus and belongs to the macrolide group of antibiotics. It is basic and readily forms salts with acids.

Erythrocin Lactobionate-IV (erythromycin lactobionate for injection, USP), is a soluble salt of erythromycin suitable for intravenous administration. It is available as a sterile, white to off-white lyophilized powder in single-dose vials. Each vial contains the equivalent of 500 mg of erythromycin activity. It is prepared as a solution and lyophilized in its final container. The lactobionic acid content is 244 mg per vial. Lactobionic acid and/or erythromycin are used to adjust the pH during the manufacture of the product. When reconstituted as directed, each mL contains 50 mg of erythromycin activity. The pH of the reconstituted solution is 6.5 - 7.5.

Erythromycin lactobionate is chemically known as erythromycin mono (4-0-β-D-galactopyranosyl-D-gluconate) (salt). The structural formula is:

CLINICAL PHARMACOLOGY

Erythromycin diffuses readily into most body fluids. In the absence of meningeal inflammation, low concentrations are normally achieved in the spinal fluid but the passage of the drug across the blood-brain barrier increases in meningitis. Erythromycin crosses the placental barrier and is excreted in breast milk. Erythromycin is not removed by peritoneal dialysis or hemodialysis.

In the presence of normal hepatic function, erythromycin is concentrated in the liver and is excreted in the bile; the effect of hepatic dysfunction on biliary excretion of erythromycin is not known. From 12 to 15 percent of intravenously administered erythromycin is excreted in active form in the urine.

Intravenous infusion of 500 mg of erythromycin lactobionate at a constant rate over 1 hour in fasting adults produced a mean serum erythromycin level of approximately 7 mcg/mL at 20 minutes, 10 mcg/mL at 1 hour, 2.6 mcg/mL at 2.5 hours, and 1 mcg/mL at 6 hours.

Microbiology

Mechanism of Action

Erythromycin acts by inhibition of protein synthesis by binding 50 S ribosomal subunits of susceptible organisms. It does not affect nucleic acid synthesis.

Resistance

Resistance to erythromycin in S. aureus may emerge during therapy. Many isolates of Haemophilus influenzae are resistant to erythromycin but are susceptible to erythromycin and sulfonamides when used concomitantly.

Interactions With Other Antimicrobials

Antagonism has been demonstrated in vitro between erythromycin and clindamycin, lincomycin and chloramphenicol.

Antimicrobial Activity

Erythromycin has been shown to be active against most isolates of the following microorganisms, both in vitro and in clinical infections (see INDICATIONS AND USAGE):

Aerobic bacteria

Gram-positive bacteria

Corynebacterium diphtheriae

Corynebacterium minutissimum

Staphylococcus aureus

Streptococcus pneumoniae

Streptococcus pyogenes

Gram-negative bacteria

Legionella pneumophila

Neisseria gonorrhoeae

Other Microorganisms

Mycoplasma pneumoniae

The following in vitro data are available, but their clinical significance is unknown. At least 90 percent of the following bacteria exhibit an in vitro minimum inhibitory concentration (MIC) less than or equal to the susceptible breakpoint for erythromycin against isolates of similar genus or organism group. However, the efficacy of erythromycin in treating clinical infections caused by these bacteria has not been established in adequate and well-controlled clinical trials.

Aerobic bacteria

Gram-negative bacteria

Moraxella catarrhalis

Susceptibility Testing

For specific information regarding susceptibility test interpretive criteria and associated test methods and quality control standards recognized by FDA for this drug, please see: https://www.fda.gov/STIC.

INDICATIONS AND USAGE

Erythrocin Lactobionate-IV (erythromycin lactobionate for injection, USP) is indicated in the treatment of infections caused by susceptible strains of the designated organisms in the diseases listed below when oral administration is not possible or when the severity of the infection requires immediate high serum levels of erythromycin. Intravenous therapy should be replaced by oral administration at the appropriate time.

Upper respiratory tract infections of mild to moderate degree caused by Streptococcus pyogenes (Group A beta-hemolytic streptococci); Streptococcus pneumoniae (Diplococcus pneumoniae); Haemophilus influenzae (when used concomitantly with adequate doses of sulfonamides, since many strains of H. influenzae are not susceptible to the erythromycin concentrations ordinarily achieved). (See appropriate sulfonamide labeling for prescribing information).

Lower respiratory tract infections of mild to moderate severity caused by Streptococcus pyogenes (Group A beta-hemolytic streptococci); Streptococcus pneumoniae (Diplococcus pneumoniae).

Respiratory tract infections due to Mycoplasma pneumoniae.

Skin and skin structure infections of mild to moderate severity caused by Streptococcus pyogenes and Staphylococcus aureus (resistant staphylococci may emerge during treatment).

Diphtheria: As an adjunct to antitoxin infections due to Corynebacterium diphtheriae to prevent establishment of carriers and to eradicate the organism in carriers.

Erythrasma: In the treatment of infections due to Corynebacterium minutissimum.

Acute pelvic inflammatory disease caused by Neisseria gonorrhoeae: Erythrocin Lactobionate-IV (erythromycin lactobionate for injection, USP) followed by erythromycin stearate or erythromycin base orally, as an alternative drug in treatment of acute pelvic inflammatory disease caused by N. gonorrhoeae in female patients with a history of sensitivity to penicillin.

Before treatment of gonorrhea, patients who are suspected of also having syphilis should have a microscopic examination for T. pallidum (by immunofluorescence or darkfield) before receiving erythromycin and monthly serologic tests for a minimum of 4 months thereafter.

Legionnaires' Disease caused by Legionella pneumophila. Although no controlled clinical efficacy studies have been conducted, in vitro and limited preliminary clinical data suggest that erythromycin may be effective in treating Legionnaires' Disease.

Prevention of Initial Attacks of Rheumatic Fever

Penicillin is considered by the American Heart Association to be the drug of choice in the prevention of initial attacks of rheumatic fever (treatment of Group A beta-hemolytic streptococcal infections of the upper respiratory tract e.g., tonsillitis, or pharyngitis).^1 Erythromycin is indicated for the treatment of penicillin-allergic patients. The therapeutic dose should be administered for ten days.

Prevention of Recurrent Attacks of Rheumatic Fever

Penicillin or sulfonamides are considered by the American Heart Association to be the drugs of choice in the prevention of recurrent attacks of rheumatic fever. In patients who are allergic to penicillin and sulfonamides, oral erythromycin is recommended by the American Heart Association in the long-term prophylaxis of streptococcal pharyngitis (for the prevention of recurrent attacks of rheumatic fever).^1

Prevention of Bacterial Endocarditis

Although no controlled clinical efficacy trials have been conducted, oral erythromycin has been recommended by the American Heart Association for prevention of bacterial endocarditis in penicillin-allergic patients with prosthetic cardiac valves, most congenital cardiac malformations, surgically constructed systemic pulmonary shunts, rheumatic or other acquired valvular dysfunction, idiopathic hypertrophic subaortic stenosis (IHSS), previous history of bacterial endocarditis and mitral valve prolapse with insufficiency when they undergo dental procedures and surgical procedures of the upper respiratory tract.^2

To reduce the development of drug-resistant bacteria and maintain the effectiveness of erythromycin and other antibacterial drugs, erythromycin should be used only to treat or prevent infections that are proven or strongly suspected to be caused by susceptible bacteria. When culture and susceptibility information are available, they should be considered in selecting or modifying antibacterial therapy. In the absence of such data, local epidemiology and susceptibility patterns may contribute to the empiric selection of therapy.

CONTRAINDICATIONS

Erythromycin is contraindicated in patients with known hypersensitivity to this antibiotic.

Erythromycin is contraindicated in patients taking terfenadine or astemizole, cisapride, pimozide, ergotamine, or dihydroergotamine (See WARNINGS and PRECAUTIONS – Drug Interactions).

Do not use erythromycin concomitantly with 3-hydroxy-3-methylglutaryl-coenzyme A (HMG CoA) reductase inhibitors (statins) that are extensively metabolized by cytochrome P450 isoform 3A4 (lovastatin or simvastatin), due to the increased risk of myopathy, including rhabdomyolysis (See WARNINGS and PRECAUTIONS – Drug Interactions).

WARNINGS

Hepatotoxicity

There have been reports of hepatic dysfunction, with or without jaundice occurring in patients receiving oral erythromycin products. Since erythromycin is principally excreted by the liver, monitor for liver toxicity when erythromycin is administered to patients with impaired hepatic function (See CLINICAL PHARMACOLOGY).

Clostridioides difficile-Associated Diarrhea

Clostridioides difficile-associated diarrhea (CDAD) has been reported with the use of nearly all antibacterial agents, including erythromycin, and may range in severity from mild diarrhea to fatal colitis. Treatment with antibacterial agents alters the normal flora of the colon, leading to overgrowth of C. difficile.

C. difficile produces toxins A and B, which contribute to the development of CDAD. Hypertoxin producing strains of C. difficile cause increased morbidity and mortality, as these infections can be refractory to antimicrobial therapy and may require colectomy. CDAD must be considered in all patients who present with diarrhea following antibiotic use. Careful medical history is necessary since CDAD has been reported to occur over 2 months after the administration of antibacterial agents.

If CDAD is suspected or confirmed, ongoing antibiotic use not directed against C. difficile may need to be discontinued. Appropriate fluid and electrolyte management, protein supplementation, antibiotic treatment of C. difficile, and surgical evaluation should be instituted as clinically indicated.

QT Prolongation

Life-threatening episodes of ventricular tachycardia associated with prolonged QT intervals (torsades de pointes) have been reported in some patients after intravenous administration of erythromycin lactobionate.

Susceptibility to the development of torsades de pointes arrhythmias, a rare but serious cardiac condition, is related to electrolyte imbalance, hepatic dysfunction, myocardial ischemia, left ventricular dysfunction, idiopathic Q-T prolongation, and concurrent antiarrhythmic therapy.^3 Elderly patients exhibit a greater frequency of decreased hepatic function, cardiac function, and of concomitant disease and other drug therapy, and therefore should be monitored carefully during ErythrocinTM therapy.

Infantile Hypertrophic Pyloric Stenosis (IHPS)

There have been reports of IHPS occurring in infants following erythromycin therapy. Since erythromycin may be used in the treatment of conditions in infants which are associated with significant mortality or morbidity (such as pertussis or chlamydia), the benefit of erythromycin therapy needs to be weighed against the potential risk of developing IHPS. Parents or caregivers of infants receiving erythromycin should be informed to contact their physician if vomiting or irritability with feeding occurs.

Drug Interactions

Serious adverse reactions have been reported in patients taking erythromycin concomitantly with CYP3A4 substrates. These include colchicine toxicity with colchicine; rhabdomyolysis with simvastatin, lovastatin, and atorvastatin; and hypotension with calcium channel blockers metabolized by CYP3A4 (e.g. verapamil, amlodipine, diltiazem, vasospasm and ischemia with ergotamine/dihydroergotamine) (See PRECAUTIONS – Drug Interactions).

PRECAUTIONS

Exacerbation of Myasthenia gravis

There have been reports that erythromycin may aggravate the weakness of patients with myasthenia gravis.

Development of Drug-Resistant Bacteria

Prolonged or repeated use of erythromycin may result in an overgrowth of non-susceptible bacteria or fungi. If superinfection occurs, erythromycin should be discontinued and appropriate therapy instituted.

When indicated, incision and drainage or other surgical procedures should be performed in conjunction with antibiotic therapy.

Prescribing erythromycin in the absence of a proven or strongly suspected bacterial infection or a prophylactic indication is unlikely to provide benefit to the patient and increases the risk of the development of drug-resistant bacteria.

Laboratory Tests

Erythromycin interferes with the fluorometric determination of urinary catecholamines.

Drug Interactions

Erythromycin administration in patients receiving 3-hydroxy-3-methylglutaryl-coenzyme A (HMG CoA) reductase inhibitors (statins) that are extensively metabolized by cytochrome P450 isoform 3A4 (e.g., lovastatin or simvastatin) has been reported to cause increased risk of myopathy, including rhabdomyolysis. Do not administer erythromycin with lovastatin or simvastatin (See CONTRAINDICATIONS).

Erythromycin use in patients who are receiving high doses of theophylline may be associated with an increase of serum theophylline levels and potential theophylline toxicity. In case of theophylline toxicity and/or elevated serum theophylline levels, the dose of theophylline should be reduced while the patient is receiving concomitant erythromycin therapy.

There have been published reports suggesting that when oral erythromycin is given concurrently with theophylline there is a significant decrease in erythromycin serum concentrations. This decrease could result in subtherapeutic concentrations of erythromycin.

Erythromycin administration in patients receiving carbamazepine has been reported to cause increased serum levels of carbamazepine with subsequent development of signs of carbamazepine toxicity.

Concomitant administration of erythromycin and digoxin has been reported to result in elevated serum digoxin levels.

There have been reports of increased anticoagulant effects, which may be more pronounced in elderly when erythromycin and oral anticoagulants (e.g., warfarin) are used concomitantly.

Colchicine is a substrate for both CYP3A4 and the efflux transporter P-glycoprotein (P-gp). Erythromycin is considered a moderate inhibitor of CYP3A4. A significant increase in colchicine plasma concentration is anticipated when co-administered with moderate CYP3A4 inhibitors such as erythromycin. If co-administration of colchicine and erythromycin is necessary, the starting dose of colchicine may need to be reduced, and the maximum colchicine dose should be lowered. Patients should be monitored for clinical symptoms of colchicine toxicity (See WARNINGS).

Erythromycin has been reported to increase the systemic exposure (AUC) of sildenafil. Reduction of sildenafil dosage should be considered (See sildenafil prescribing information).

Erythromycin has been reported to decrease the clearance of triazolam, midazolam and related benzodiazepines, and thus may increase the pharmacological effect of these benzodiazepines.

Post-marketing reports indicate that co-administration of erythromycin with ergotamine or dihydroergotamine has been associated with acute ergot toxicity characterized by vasospasm and ischemia of the central nervous system, extremities and other tissues (See CONTRAINDICATIONS).

Erythromycin has been reported to significantly alter the metabolism of the nonsedating antihistamines, terfenadine and astemizole, when taken concomitantly. Rare cases of serious cardiovascular adverse events, including electrocardiographic QT/QTc interval prolongation, cardiac arrest, torsades de pointes, and other ventricular arrhythmias, have been observed (See CONTRAINDICATIONS). In addition, deaths have been reported rarely with concomitant administration of terfenadine and erythromycin.

The use of erythromycin in patients concurrently taking drugs metabolized by the cytochrome P450 system may be associated with elevations in serum levels of these other drugs. There have been reports of interactions of erythromycin with carbamazepine, cyclosporine, hexobarbital, phenytoin, alfentanil, disopyramide, bromocriptine, valproate, terfenadine, and astemizole. Serum concentrations of drugs metabolized by the cytochrome P450 system should be monitored closely in patients concurrently receiving erythromycin.

Hypotension, bradyarrhythmias and lactic acidosis have been observed in patients receiving concurrent verapamil, a calcium-channel blocker.

Cimetidine may inhibit the metabolism of erythromycin, which may lead to an increased plasma concentration.

Erythromycin has been reported to decrease the clearance of racemic zopiclone and, thus, may also decrease the clearance of eszopiclone, the S-enantiomer of racemic zopiclone. Accordingly, erythromycin may increase the pharmacodynamic effects of eszopiclone. Dose reduction of eszopiclone may be necessary (See eszopiclone prescribing information).

Carcinogenesis, Mutagenesis, Impairment of Fertility

Long-term animal data with erythromycin lactobionate for use in determination of possible carcinogenic effects are not available. However, long-term oral studies in rats with erythromycin ethylsuccinate and erythromycin base did not provide evidence of tumorigenicity. Mutagenicity studies have not been conducted. There was no apparent effect on male or female fertility in rats fed erythromycin (base) at levels up to 0.25% of diet.

Pregnancy

There was no evidence of teratogenicity or any other adverse effect on reproduction in female rats fed erythromycin base (up to 0.25% of diet) prior to and during mating, during gestation, and through weaning of two successive litters. There are, however, no adequate and well-controlled studies in pregnant women. Because animal reproduction studies are not always predictive of human response, this drug should be used during pregnancy only if clearly needed. Erythromycin has been reported to cross the placental barrier in humans, but fetal plasma levels are generally low.

Labor and Delivery

The effect of erythromycin on labor and delivery is unknown.

Nursing Mothers

Erythromycin is excreted in breast milk. Caution should be exercised when erythromycin is administered to a nursing woman.

Pediatric Use

(See INDICATIONS AND USAGE and DOSAGE AND ADMINISTRATION).

Geriatric Use

Elderly patients, particularly those with reduced renal or hepatic function, may be at increased risk for developing erythromycin-induced hearing loss, when ErythrocinTM doses of 4 grams/day or higher are given (See ADVERSE REACTIONS and DOSAGE AND ADMINISTRATION).

Elderly patients may be more susceptible to the development of torsades de pointes arrhythmias than younger patients (See ADVERSE REACTIONS).

Elderly patients may experience increased effects of oral anticoagulant therapy while undergoing treatment with ErythrocinTM (See PRECAUTIONS – Drug Interactions).

Erythromycin Lactobionate does not contain sodium.

Information for Patients

Patients should be counseled that antibacterial drugs including erythromycin should only be used to treat bacterial infections. They do not treat viral infections (e.g., the common cold). When erythromycin is prescribed to treat a bacterial infection, patients should be told that although it is common to feel better early in the course of therapy, the medication should be taken exactly as directed. Skipping doses or not completing the full course of therapy may (1) decrease the effectiveness of the immediate treatment and (2) increase the likelihood that bacteria will develop resistance and will not be treatable by erythromycin or other antibacterial drugs in the future.

Diarrhea is a common problem caused by antibiotics which usually ends when the antibiotic is discontinued. Sometimes after starting treatment with antibiotics, patients can develop watery and bloody stools (with or without stomach cramps and fever) even as late as two or more months after having taken the last dose of the antibiotic. If this occurs, patients should contact their physician as soon as possible.

ADVERSE REACTIONS

Erythromycin has been associated with QT prolongation and ventricular arrhythmias, including ventricular tachycardia and torsades de pointes (See WARNINGS).

Side effects following the use of intravenous erythromycin are rare. Occasional venous irritation has been encountered, but if the infusion is given slowly, in dilute solution, preferably by continuous intravenous infusion or intermittent infusion in no less than 20 to 60 minutes, pain and vessel trauma are minimized.

Allergic reactions ranging from urticaria to anaphylaxis have occurred. Skin reactions ranging from mild eruptions to erythema multiforme, Stevens-Johnson syndrome, and toxic epidermal necrolysis have been reported rarely.

There have been isolated reports of reversible hearing loss occurring chiefly in patients with renal insufficiency and in patients receiving high doses of erythromycin.

Elderly patients, particularly those with reduced renal or hepatic function, may also be at increased risk for developing this effect when ErythrocinTM doses of 4 grams/day or higher are given (See DOSAGE AND ADMINISTRATION).

OVERDOSAGE

In the case of overdosage, erythromycin infusion should be discontinued and all other appropriate measures should be instituted. Adverse reactions at higher than recommended doses could be similar to those reported with oral formulations of erythromycin, particularly, severe abdominal pain, nausea, vomiting, diarrhea, hepatitis, pancreatitis, and transient hearing loss.

Erythromycin is not removed by peritoneal dialysis or hemodialysis.

DOSAGE AND ADMINISTRATION

For the treatment of severe infections in adults and pediatric patients, the recommended intravenous dose of erythromycin lactobionate is 15 to 20 mg/kg/day. Higher doses, up to 4 g/day, may be given for severe infections.

Administration of doses of ≥4 g/day may increase the risk for the development of erythromycin-induced hearing loss in elderly patients, particularly those with reduced renal or hepatic function. Erythrocin Lactobionate-IV (erythromycin lactobionate for injection, USP) must be administered by continuous or intermittent intravenous infusion only. Due to the irritative properties of erythromycin, IV push is an unacceptable route of administration.

Continuous infusion of erythromycin lactobionate is preferable due to the slower infusion rate and lower concentration of erythromycin; however, intermittent infusion at six hour intervals is also effective. Intravenous erythromycin should be replaced by oral erythromycin as soon as possible.

For slow continuous infusion: The final diluted solution of erythromycin lactobionate is prepared to give a concentration of 1 g per liter (1 mg/mL).

For intermittent infusion: Administer one-fourth the total daily dose of erythromycin lactobionate by intravenous infusion in 20 to 60 minutes at intervals not greater than every six hours. The final diluted solution of erythromycin lactobionate is prepared to give a concentration of 1 to 5 mg/mL. No less than 100 mL of IV diluent should be used. Infusion should be sufficiently slow to minimize pain along the vein.

For treatment of acute pelvic inflammatory disease caused by N. Gonorrhoeae, in female patients hypersensitive to penicillins, administer 500 mg erythromycin lactobionate every six hours for three days, followed by oral administration of 250 mg erythromycin stearate or base every six hours for seven days.

For treatment of Legionnaires' Disease: Although optimal doses have not been established, doses utilized in reported clinical data were 1 to 4 grams daily in divided doses.

Administration of doses of ≥ 4 g/day may increase the risk for the development of erythromycin-induced hearing loss in elderly patients, particularly those with reduced renal or hepatic function.

In the treatment of Group A beta-hemolytic streptococcal infections of the upper respiratory tract (e.g., tonsillitis or pharyngitis), the therapeutic dosage of erythromycin should be administered for ten days. The American Heart Association suggests a dosage of 250 mg of erythromycin orally, twice a day in long-term prophylaxis of streptococcal upper respiratory tract infections for the prevention of recurring attacks of rheumatic fever in patients allergic to penicillin and sulfonamides.^1

In prophylaxis against bacterial endocarditis (See INDICATIONS AND USAGE) the oral regimen for penicillin allergic patients is erythromycin 1 gram, 1 hour before the procedure followed by 500 mg six hours later.^2

Preparation of Solution:

Erythrocin Lactobionate-IV is a lyophilized powder, which requires reconstitution and further dilution before administration according to the steps below:

1. Reconstitute Erythrocin Lactobionate-IV by adding 10 mL of Sterile Water for Injection, USP to the 500 mg single-dose vial to give a concentration of 50 mg of erythromycin activity per milliliter (50 mg/mL). Do not use other diluents in this step because other diluents may cause precipitation during reconstitution. Do not use diluents containing preservatives or inorganic salts. The reconstituted solution is stable at refrigerator temperature for 2 weeks, or for 24 hours at room temperature.

2. Add the reconstituted solution to one of the following diluents before administration to give a concentration of 1 g of erythromycin activity per liter (1 mg/mL) for continuous infusion or 1 to 5 mg/mL for intermittent infusion:

• 0.9% Sodium Chloride Injection, USP

• Lactated Ringer’s Injection, USP

• NormosolTM-R.

Do not use other diluents in this step 2. Acidic solutions of Erythrocin Lactobionate-IV (solutions with a pH < 5.5) are unstable and lose their potency rapidly.

Do not add any drug or chemical agent to an erythromycin lactobionate-IV solution unless its effect on the chemical and physical stability of the solution has first been determined.

Stability

The final diluted solution of erythromycin lactobionate should be completely administered within 8 hours, since it is not suitable for storage. Discard unused portion.

Parenteral drug products should be inspected visually for particulate matter and discoloration prior to administration, whenever solution and container permit.

HOW SUPPLIED

Erythrocin Lactobionate-IV (erythromycin lactobionate for injection, USP) is supplied as a sterile, white to off-white lyophilized powder as follows:

Unit of Sale | Concentration
NDC 0409-6482-01; Tray of 10 single-dose vials | 500 mg/vial

Store at 20 to 25ºC (68 to 77ºF). [See USP Controlled Room Temperature].

REFERENCES

1. Committee on Rheumatic Fever and Infective Endocarditis of the Council on Cardiovascular Disease of the Young: Prevention of Rheumatic Fever, Circulation 70(6):1118A-1122A, December 1984.
2. Committee on Rheumatic Fever and Infective Endocarditis of the Council on Cardiovascular Disease of the Young: Prevention of Bacterial Endocarditis, Circulation 70(6):1123A-1127A, December 1984.
3. Gilter, B., et al, Torsades de Pointes Induced by Erythromycin, Chest, Volume 105: 368-72, February 1994.

Distributed by Hospira, Inc., Lake Forest, IL 60045 USA

LAB-1218-6.0

Revised: 11/2022

PRINCIPAL DISPLAY PANEL - 500 mg Vial Label

Sterile Powder
For Injection

NDC 0409-6482-11
Single-dose vial

ERYTHROCIN™ Lactobionate-I.V.
Erythromycin Lactobionate for Injection, USP

Erythromycin Activity
500 mg/vial

Benzyl Alcohol Free Formula

Discard unused portion.
Dist. by Hospira, Inc. Lake Forest, IL 60045 USA
Rx only

PRINCIPAL DISPLAY PANEL - 500 mg Vial Tray

10 Single-dose vials
Sterile Powder for Injection

NDC 0409-6482-01
Rx only

ERYTHROCIN™ Lactobionate - I.V.

Erythromycin Lactobionate for Injection, USP

Erythromycin Activity
500 mg/vial

FOR INTRAVENOUS USE ONLY.
Benzyl Alcohol Free Formula

Hospira